DRUG LABEL: Hydrocortisone 1%
NDC: 57896-146 | Form: CREAM
Manufacturer: Geri-Care Pharmaceuticals, Corp
Category: otc | Type: HUMAN OTC DRUG LABEL
Date: 20241217

ACTIVE INGREDIENTS: HYDROCORTISONE 1 g/100 g
INACTIVE INGREDIENTS: PHENOXYETHANOL; MINERAL OIL; GLYCERIN; GLYCERYL MONOSTEARATE; PETROLATUM; WATER; POLYOXYL 20 CETOSTEARYL ETHER; CETOSTEARYL ALCOHOL; ETHYLHEXYLGLYCERIN

Geri-Care Hydrocortisone Cream 1%
MAXIMUM STRENGTH

Active ingredient

Hydrocortisone 1%

Purpose

Antipruritic (Anti-Itch)

Keep out of the reach of children.

If swallowed, get medical help or contact a Poison Control Center immediately.

Uses

For temporary relief of itching associated with minor skin irritations and rashes

● external feminine, genital and anal itching

Other uses of this product should be only under the advice and supervision of a doctor

Do Not Use

- For the treatment of diaper rash, consult a doctor.
- With any other Hydrocortisone product unless you have consulted a doctor
- If you have a vaginal discharge, consult a doctor

Warnings

For external use only

When using this product

- Avoid Contact with the eyes
- do not exceed the recommended daily dosage unless directed by a doctor.
- do not put this product into the rectum by using fingers or any mechanical device or applicator.

Stop using this product and ask a doctor if

- conditions worsens, symptoms persist for more than 7 days or symptoms clear up and reappear again within a few days.
- Discontinue use of this product and do not begin use of any other hydrocortisone product unless directed by a doctor.
- Rectal bleeding occurs

Directions

For Itching or skin irritation, inflammation, and rashes:

Adults and children 2 years of age and older: apply to the affected area not more than 3 to 4 times daily.

Children under 2 years of age: do not use and ask a doctor.

For External and anal itching in adults:

When practical, clean affected area with mild soap and warm water and rinse thoroughly

Gently dry by patting or blotting with toilet tissue or a soft cloth before applying

apply to affected area not more than 3 to 4 times daily.

For children under 12 years of age: Ask a doctor

Inactive ingredients

Ceteareth-20, Cetearyl alcohol, Ethylhexylglycerin, Glycerin, Glyceryl Stearate, mineral oil, petrolatum, Phenoxyethanol, water.

Other information

● store at controlled room temperature 20°-25°C (68 °- 77 °F)

Tamper evident, do not use if packet is torn, cut or opened.

Avoid excessive heat and humidity.

Questions

Call 1-800-540-3765

Distributed By

Geri-Care Pharmaceuticals Corp

1295 Towbin Ave.

Lakewood, NJ 08701